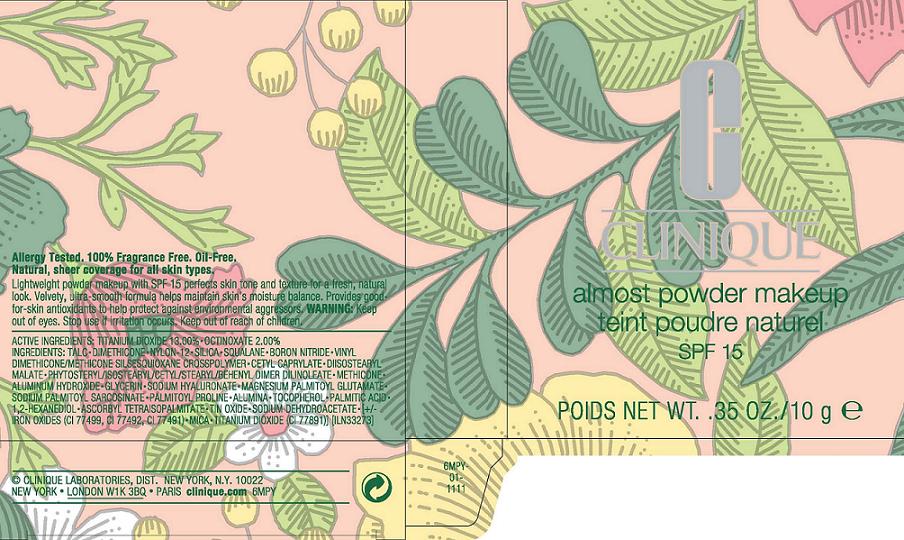 DRUG LABEL: ALMOST POWDER MAKEUP
NDC: 49527-800 | Form: POWDER
Manufacturer: CLINIQUE LABORATORIES INC
Category: otc | Type: HUMAN OTC DRUG LABEL
Date: 20110621

ACTIVE INGREDIENTS: TITANIUM DIOXIDE 13.0 g/100 g; OCTINOXATE 2.0 g/100 g
INACTIVE INGREDIENTS: TALC; DIMETHICONE; SILICON DIOXIDE; SQUALANE; BORON NITRIDE; CETYL OCTANOATE; ALUMINUM HYDROXIDE; GLYCERIN; HYALURONATE SODIUM; SODIUM PALMITOYL GLUTAMATE; ALUMINUM OXIDE; TOCOPHEROL; PALMITIC ACID; HEXANEDIOL; ASCORBYL PALMITATE; TIN; SODIUM DEHYDROACETATE; FERRIC OXIDE RED; MICA

ACTIVE INGREDIENT

active ingredients: titanium dioxide 13.00% [] octinoxate 2.00%

INACTIVE INGREDIENT

inactive ingredients: talc [] dimethicone [] nylon-12 [] silica [] squalane [] boron nitride [] vinyl dimethicone/methicone silsesquioxane crosspolymer [] cetyl caprylate [] diisostearyl malate [] phytosteryl/isostearyl/cetyl/stearyl/behenyl dimer dilinoleate [] methicone [] aluminum hydroxide [] glycerin [] sodium hyaluronate [] magnesium palmitoyl glutamate [] sodium palmitoyl sarcosinate [] palmitoyl proline [] alumina [] tocopherol [] palmitic acid [] 1,2-hexanediol [] ascorbyl tetraisopalmitate [] tin oxide [] sodium dehydroacetate [] [+/- iron oxides (ci 77499, ci 77492, ci 77491) [] mica [] titanium dioxide (ci 77891)]

WARNINGS

warning: keep out of eyes. stop use if irritation occurs. keep out of reach of children.

PACKAGE LABEL

principal display panel:

CLINIQUE

ALMOST POWDER MAKEUP

SPF 15

NT WT. 0.35 OZ/ 10 g
clinique laboratories dist.
new york, ny 10022